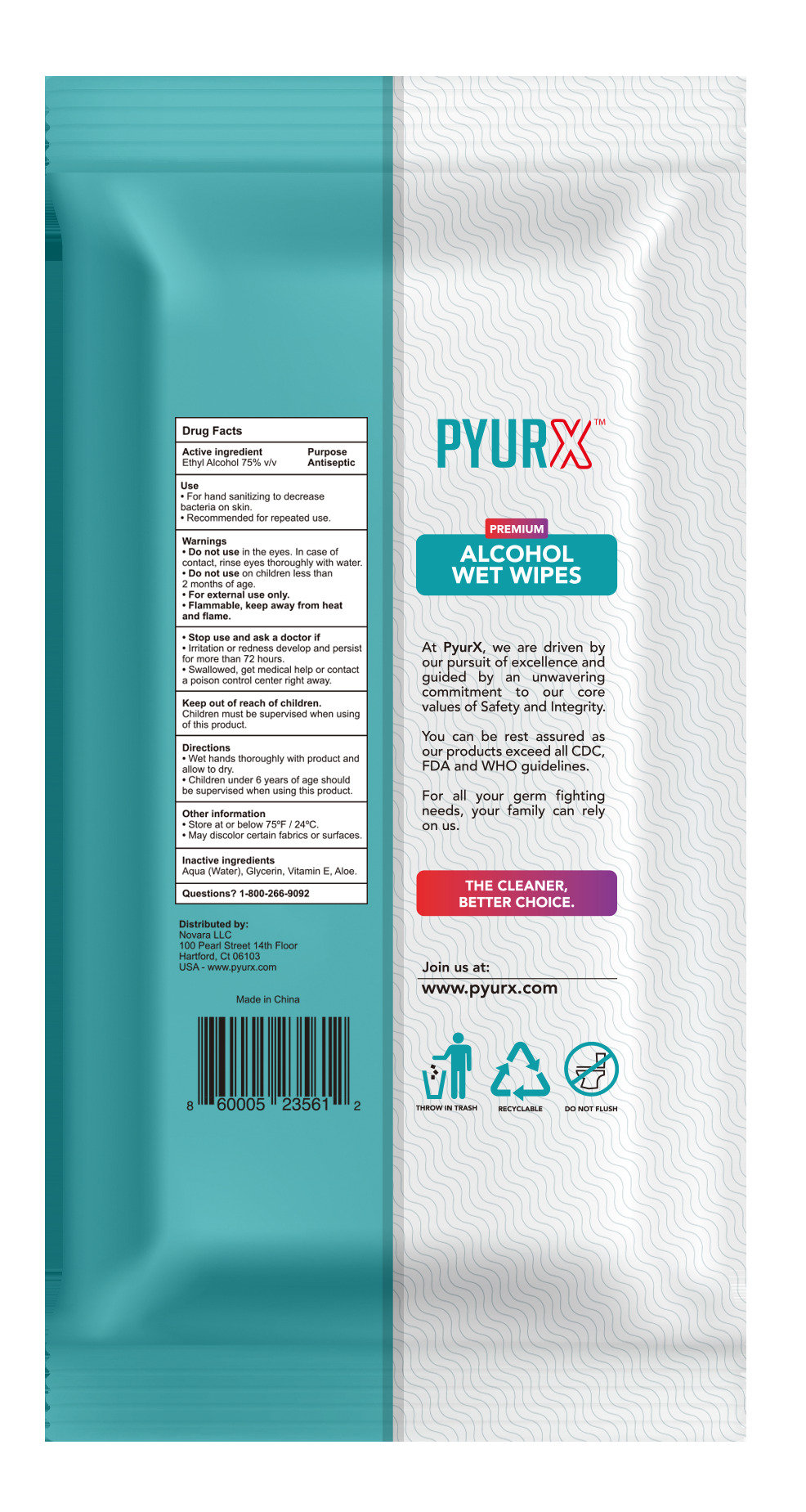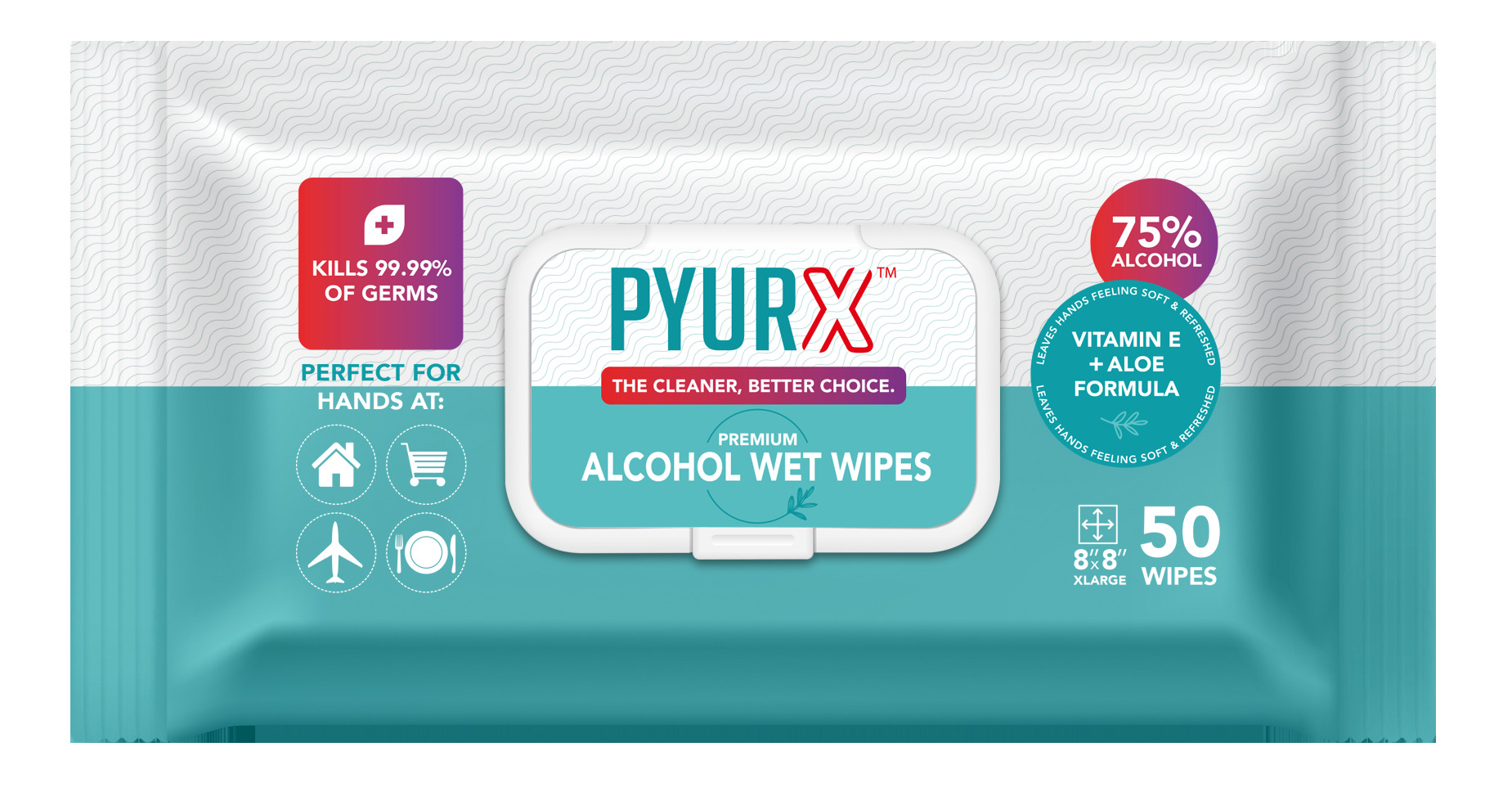 DRUG LABEL: PyurX
NDC: 80527-351 | Form: CLOTH
Manufacturer: Novara LLC
Category: otc | Type: HUMAN OTC DRUG LABEL
Date: 20210208

ACTIVE INGREDIENTS: ALCOHOL 75 mL/100 mL
INACTIVE INGREDIENTS: GLYCERIN 0.3 mL/100 mL; ALPHA-TOCOPHEROL ACETATE 0.4 mL/100 mL; WATER 24 mL/100 mL; ALOE 0.3 mL/100 mL

75% Alcohol Disinfectant Wet Wipes. 50 count

Active Ingredient(s)

Ethyl Alcohol 75% v/v. Purpose: Antiseptic

Purpose

Antiseptic, Hand Sanitizing

Use

- For hand sanitizing to decrease bacteria on skin.
- Recommened for repeated use.

Warnings

- Do not use in the eyes. In case of contact, rinse eyes thoroughly with water.
- Do not use on children less than 2 months of age.
- For external use only.
- Flammable Keep away from heat or flame

- Do not use in the eyes. In case of contact, rinse thoroughly with water.
- Do not use on children less than 2 months of age.

- Stop use and ask a doctor if irritation or redness develop and persist for more than 72 hours.
- Swallowed, get medical help or contact a poison control center right away.

Keep out of reach of children

- Children must be supervised when using this product.

Directions

- Wet hands thoroughly with product and allow to dry.
- Children under 6 years of age should be supervised when using this product.

Other information

- Store at below or below 75F (24C).
- May discolor certain fabrics or surfaces.

Inactive ingredients

glycerin, Aqua(water), Vitamin E, Aloe